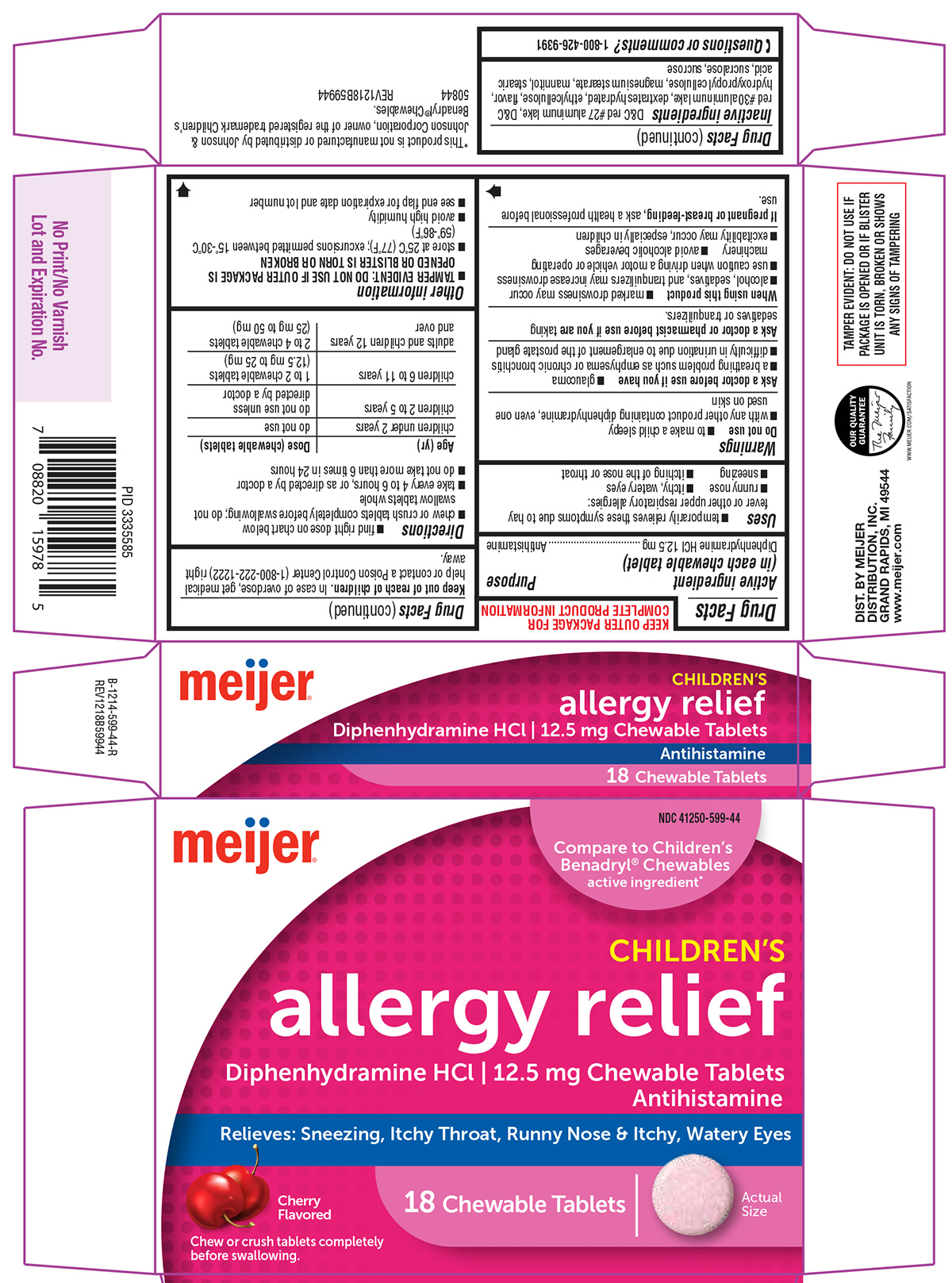 DRUG LABEL: Allergy Relief
NDC: 41250-599 | Form: TABLET, CHEWABLE
Manufacturer: Meijer Distribution Inc
Category: otc | Type: HUMAN OTC DRUG LABEL
Date: 20250903

ACTIVE INGREDIENTS: DIPHENHYDRAMINE HYDROCHLORIDE 12.5 mg/1 1
INACTIVE INGREDIENTS: D&C RED NO. 27 ALUMINUM LAKE; D&C RED NO. 30 ALUMINUM LAKE; DEXTROSE MONOHYDRATE; ETHYLCELLULOSE, UNSPECIFIED; HYDROXYPROPYL CELLULOSE, UNSPECIFIED; MAGNESIUM STEARATE; MANNITOL; STEARIC ACID; SUCRALOSE; SUCROSE

Meijer 44-599

Active ingredient (in each chewable tablet)

Diphenhydramine HCl 12.5 mg

Purpose

Antihistamine

Uses

- temporarily relieves these symptoms due to hay fever or other upper respiratory allergies:
  - runny nose
  - itchy, watery eyes
  - sneezing
  - itching of the nose or throat

Warnings

Do not use

- to make a child sleepy
- with any other product containing diphenhydramine, even one used on skin

Ask a doctor before use if you have

- glaucoma
- a breathing problem such as emphysema or chronic bronchitis
- difficulty in urination due to enlargement of the prostate gland

Ask a doctor or pharmacist before use if you are

taking sedatives or tranquilizers.

When using this product

- marked drowsiness may occur
- alcohol, sedatives, and tranquilizers may increase drowsiness
- use caution when driving a motor vehicle or operating machinery
- avoid alcoholic beverages
- excitability may occur, especially in children

If pregnant or breast-feeding,

ask a health professional before use.

Keep out of reach of children.

In case of overdose, get medical help or contact a Poison Control Center (1-800-222-1222) right away.

Directions

- find right dose on chart below
- chew or crush tablets completely before swallowing; do not swallow tablets whole
- take every 4 to 6 hours, or as directed by a doctor
- do not take more than 6 times in 24 hours

Age (yr) | Dose (chewable tablets)
children under 2 years | do not use
children 2 to 5 years | do not use unless directed by a doctor
children 6 to 11 years | 1 to 2 chewable tablets (12.5 mg to 25 mg)
adults and children 12 years and over | 2 to 4 chewable tablets (25 mg to 50 mg)

Other information

- TAMPER EVIDENT: DO NOT USE IF OUTER PACKAGE IS OPENED OR BLISTER IS TORN OR BROKEN
- store at 25ºC (77ºF); excursions permitted between 15º-30ºC (59º-86ºF)
- avoid high humidity
- see end flap for expiration date and lot number

Inactive ingredients

D&C red #27 aluminum lake, D&C red #30 aluminum lake, dextrates hydrated, ethylcellulose, flavor, hydroxypropyl cellulose, magnesium stearate, mannitol, stearic acid, sucralose, sucrose

Questions or comments?

1-800-426-9391

Principal Display Panel

meijer®

NDC 41250-599-44

Compare to Children's
Benadryl® Chewables
active ingredient*

CHILDREN'S
allergy relief
Diphenhydramine HCl | 12.5 mg Chewable Tablets
Antihistamine

Relieves: Sneezing, Itchy Throat, Runny Nose & Itchy, Watery Eyes

Cherry
Flavored

18 Chewable Tablets

Actual
Size

Chew or crush tablets completely
before swallowing.

TAMPER EVIDENT: DO NOT USE IF
PACKAGE IS OPENED OR IF BLISTER
UNIT IS TORN, BROKEN OR SHOWS
ANY SIGNS OF TAMPERING

DIST. BY MEIJER
DISTRIBUTION, INC.
GRAND RAPIDS, MI 49544
www.meijer.com

OUR QUALITY
GUARANTEE
The Meijer
Family
WWW.MEIJER.COM/SATISFACTION

*This product is not manufactured or distributed by Johnson &
Johnson Corporation, owner of the registered trademark Children's
Benadryl® Chewables.

50844 REV1218B59944

Meijer 44-599